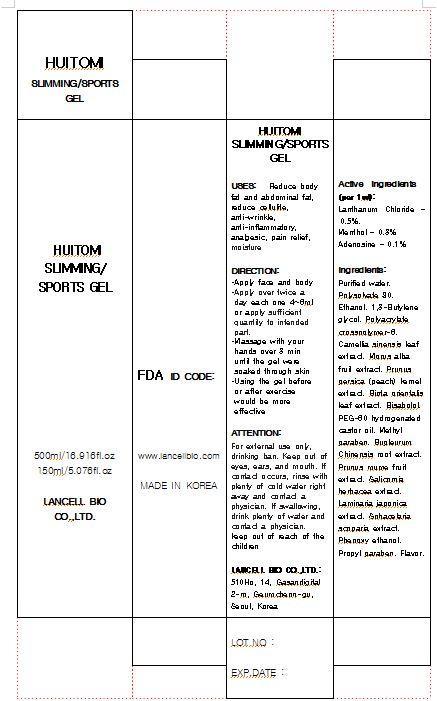 DRUG LABEL: HUITOMI SLIMMING SPORTS
NDC: 69388-4001 | Form: GEL
Manufacturer: Lancell Bio Co., Ltd.
Category: otc | Type: HUMAN OTC DRUG LABEL
Date: 20141201

ACTIVE INGREDIENTS: MENTHOL 0.3 g/100 mL
INACTIVE INGREDIENTS: WATER; LANTHANUM CHLORIDE; ADENOSINE

Drug Facts

ACTIVE INGREDIENT

menthol

INACTIVE INGREDIENT

■Purified water ■Polysolvate 80 ■Ethanol ■1,3-Butylene glycol ■Polyacrylate crosspolymer-6 ■Camellia sinensis leaf extract ■Morus alba fruit extract ■Prunus persica (peach) kernel extract ■Biota orientalis leaf extract ■Bisabolol ■PEG-60 hydrogenated castor oil ■Methyl paraben ■Bupleurum Chinensis root extract ■Prunus mume fruit extract ■Salicornia herbacea extract ■Laminaria japonica extract ■Sphacelaria scoparia extract ■Phenoxy ethanol ■Propyl paraben ■Flavor

PURPOSE

reduce body fat and abdominal fat
reduce cellulite
anti-wrinkle
anti-imflammatory
analgesic
pain relief
moisture

keep out of reach of children

INDICATIONS AND USAGE

This product is only used to manage your site, such as fat or forearm and thigh and can be applied to all parts of the body except the face and chest, but use the small sensitive area.
Squeeze the required amount of gel in the palm when applied to the skin after 2 or 3 minutes and cool or warm feeling occurs; we recommend you so sweaty moderate exercise to the body as possible. After applying the gel is also recommended to use the sauna or electric massager aids such as hula hoops.
If using this product on part that use a lot of muscle or joint before or after exercise prevent arthralgia and myalgia or restore tired muscle and joint rapidly

WARNINGS

For external use only, drinking ban
keep in a cool place

DOSAGE AND ADMINISTRATION

for external use only